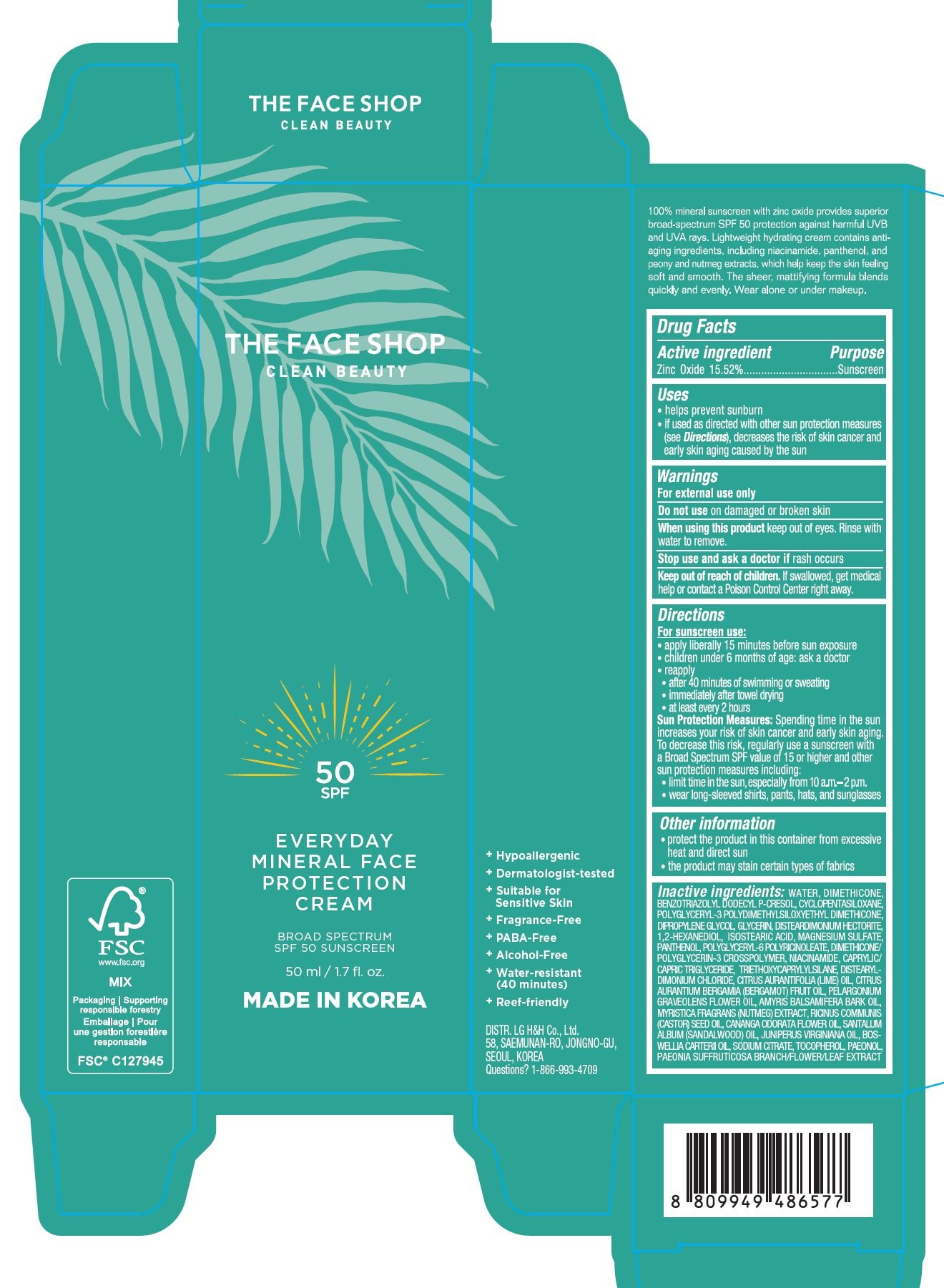 DRUG LABEL: THE FACE SHOP EVERYDAY MINERAL FACE PROTECTION SPF 50
NDC: 72330-151 | Form: CREAM
Manufacturer: fmg Co.Ltd
Category: otc | Type: HUMAN OTC DRUG LABEL
Date: 20240201

ACTIVE INGREDIENTS: ZINC OXIDE 15.52 g/50 mL
INACTIVE INGREDIENTS: WATER

THE FACE SHOP EVERYDAY MINERAL FACE PROTECTION CREAM SPF 50

ACTIVE INGREDIENTS

Zinc Oxide 15.52%

PURPOSE

Sunscreen

USES

- helps prevent sunburn
- if used as directed with other sun protection measures (see Directions), decreases the risk of skin cancer and early skin aging caused by the sun

WARNINGS

For external use only

- Do not use on damaged or broken skin

- When using this product keep out of eyes. Rinse with water to remove.

- Stop use and ask a doctor if rash occurs

- Keep out of reach of children. If swallowed, get medical help or contact a Poison Control Center right away.

DIRECTIONS

For sunscreen use:

- apply liberally 15 minutes before sun exposure
- children under 6 months of age: ask a doctor
- reapply
- - after 40 minutes of swimming or sweating
- - immediately after towel drying
- - at least every 2 hours

Sun Protection Measures: Spending time in the sun increases your risk of skin cancer and early skin aging. To decrease this risk, regularly use a sunscreen with a Broad Spectrum SPF value of 15 or higher and other sun protection measures including:

- limit time in the sun, especially from 10 a.m.-2 p.m.
- wear long-sleeved shirts, pants, hats, and sunglasses

OTHER INFORMATION

- protect the product in this container from excessive heat and direct sun
- the product may stain certain types of fabrics

INACTIVE INGREDIENTS

WATER

QUESTIONS?

1-866-993-4709

+ Hypoallergenic

+ Dermatologist-tested

+ Suitable for Sensitive Skin
+ Fragrance-Free
+ PABA-Free
+ Alcohol-Free
+ Water-resistant (40 minutes)
+ Reef-friendly

DISTR. LG H&H Co., Ltd.
58, SAEMUNAN-RO, JONGNO-GU,
SEOUL, KOREA
Questions? 1-866-993-4709

100% mineral sunscreen with zinc oxide provides superior broad-spectrum SPF 50 protection against harmful UVB and UVA rays. Lightweight hydrating cream contains anti-aging ingredients, including niacinamide, panthenol, and peony and nutmeg extracts, which help keep the skin feeling soft and smooth. The sheer, mattifying formula blends quickly and evenly. Wear alone or under makeup.

PRINCIPAL DISPLAY PANEL

THE FACE SHOP

CLEAN BEAUTY

50
SPF

EVERYDAY
MINERAL FACE
PROTECTION
CREAM

BROAD SPECTRUM
SPF 50 SUNSCREEN

50 ml / 1.7 fl.oz.

MADE IN KOREA